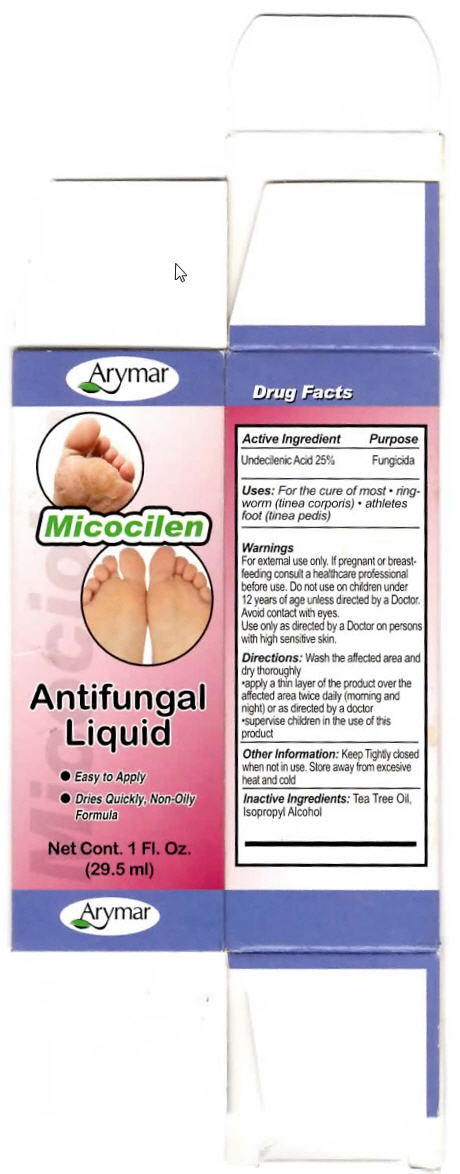 DRUG LABEL: Micocilen 
NDC: 70570-0199 | Form: LIQUID
Manufacturer: Arymar Inc.
Category: otc | Type: HUMAN OTC DRUG LABEL
Date: 20190304

ACTIVE INGREDIENTS: Undecylenic Acid 250 mg/1 mL
INACTIVE INGREDIENTS: Tea Tree Oil; Isopropyl Alcohol

Micocilen
Antifungal

Drug Facts

Active Ingredient

Undecilenic Acid 25%

Purpose

Fungicida

Uses

For the cure of most

- ringworm (tinea corporis)
- athletes foot (tinea pedis)

Warnings

For external use only. If pregnant or breastfeeding consult a healthcare professional before use.

Do not use on children under 12 years of age unless directed by a Doctor. Avoid contact with eyes.

Use only as directed by a Doctor on persons with high sensitive skin.

Directions

Wash the affected area and dry thoroughly

- apply a thin layer of the product over the affected area twice daily (morning and night) or as directed by a doctor
- supervise children in the use of this product

Other Information

Keep Tightly closed when not in use. Store away from excessive heat and cold

Inactive Ingredients

Tea Tree Oil, Isopropyl Alcohol

PRINCIPAL DISPLAY PANEL - 29.5 ml Vial Carton

Arymar

Micocilen

Antifungal
Liquid

- Easy to Apply
- Dries Quickly, Non-Oily
  Formula

Net Cont. 1 Fl. Oz.
(29.5 ml)

Arymar